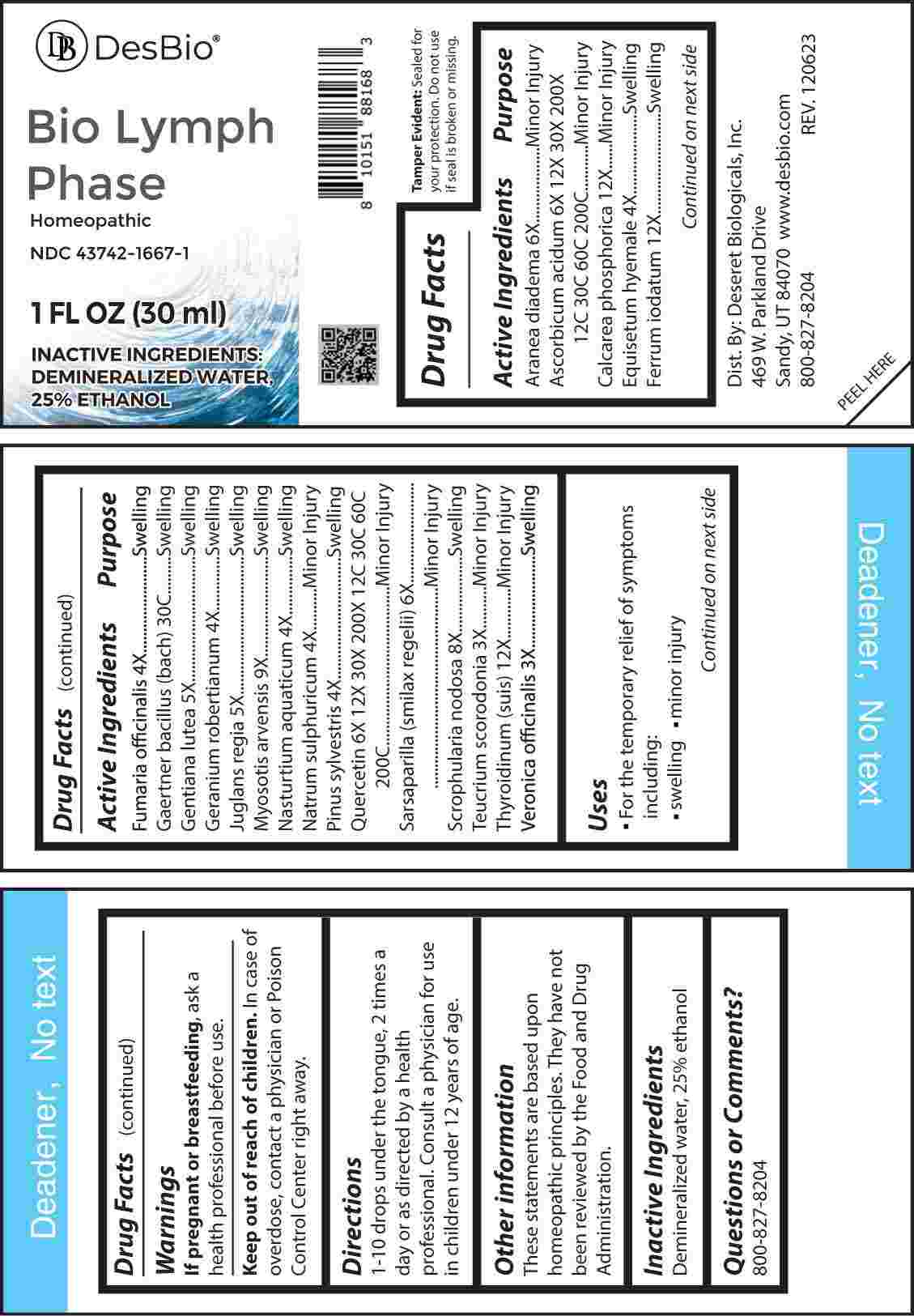 DRUG LABEL: Bio Lymph Phase
NDC: 43742-1667 | Form: LIQUID
Manufacturer: Deseret Biologicals, Inc.
Category: homeopathic | Type: HUMAN OTC DRUG LABEL
Date: 20240315

ACTIVE INGREDIENTS: TEUCRIUM SCORODONIA FLOWERING TOP 3 [hp_X]/1 mL; VERONICA OFFICINALIS FLOWERING TOP 3 [hp_X]/1 mL; EQUISETUM HYEMALE WHOLE 4 [hp_X]/1 mL; FUMARIA OFFICINALIS FLOWERING TOP 4 [hp_X]/1 mL; GERANIUM ROBERTIANUM WHOLE 4 [hp_X]/1 mL; NASTURTIUM OFFICINALE 4 [hp_X]/1 mL; SODIUM SULFATE 4 [hp_X]/1 mL; PINUS SYLVESTRIS LEAFY TWIG 4 [hp_X]/1 mL; GENTIANA LUTEA ROOT 5 [hp_X]/1 mL; JUGLANS REGIA LEAF 5 [hp_X]/1 mL; ARANEUS DIADEMATUS 6 [hp_X]/1 mL; SMILAX ORNATA ROOT 6 [hp_X]/1 mL; ASCORBIC ACID 6 [hp_X]/1 mL; QUERCETIN 6 [hp_X]/1 mL; SCROPHULARIA NODOSA WHOLE 8 [hp_X]/1 mL; MYOSOTIS ARVENSIS WHOLE 9 [hp_X]/1 mL; TRIBASIC CALCIUM PHOSPHATE 12 [hp_X]/1 mL; FERROUS IODIDE 12 [hp_X]/1 mL; THYROID 12 [hp_X]/1 mL; SALMONELLA ENTERICA ENTERICA SEROVAR ENTERITIDIS 30 [hp_C]/1 mL
INACTIVE INGREDIENTS: WATER; ALCOHOL

DRUG FACTS:

ACTIVE INGREDIENTS:

Aranea Diadema 6X, Ascorbicum Acidum 6X, 12X, 30X, 200X, 12C, 30C, 60C, 200C, Calcarea Phosphorica 12X, Equisetum Hyemale 4X, Ferrum Iodatum 12X, Fumaria Officinalis 4X, Gaertner Bacillus (Bach) 30C, Gentiana Lutea 5X, Geranium Robertianum 4X, Juglans Regia 5X, Myosotis Arvensis 9X, Nasturtium Aquaticum 4X, Natrum Sulphuricum 4X, Pinus Sylvestris 4X, Quercetin 6X, 12X, 30X, 200X, 12C, 30C, 60C, 200C, Sarsaparilla (Smilax Regelii) 6X, Scrophularia Nodosa 8X, Teucrium Scorodonia 3X, Thyroidinum (Suis) 12X, Veronica Officinalis 3X.

PURPOSE:

Aranea Diadema – Minor Injury, Ascorbicum Acidum – Minor Injury, Calcarea Phosphorica – Minor Injury, Equisetum Hyemale - Swelling, Ferrum Iodatum - Swelling, Fumaria Officinalis - Swelling, Gaertner Bacillus (Bach) - Swelling, Gentiana Lutea - Swelling, Geranium Robertianum - Swelling, Juglans Regia - Swelling, Myosotis Arvensis – Swelling, Nasturtium Aquaticum - Swelling, Natrum Sulphuricum – Minor Injury, Pinus Sylvestris - Swelling, Quercetin – Minor Injury, Sarsaparilla (Smilax Regelii) – Minor Injury, Scrophularia Nodosa - Swelling, Teucrium Scorodonia – Minor Injury, Thyroidinum (Suis) – Minor Injury, Veronica Officinalis - Swelling

USES:

• For the temporary relief of symptoms including:

• swelling • minor injury

These statements are based upon homeopathic principles. They have not been reviewed by the Food and Drug Administration.

WARNINGS:

If pregnant or breast-feeding, ask a health professional before use.

Keep out of reach of children. In case of overdose, contact a physician or Poison Control Center right away.

Tamper Evident: Sealed for your protection. Do not use if seal is broken or missing.

KEEP OUT OF REACH OF CHILDREN:

In case of overdose, contact a physician or Poison Control Center right away.

DIRECTIONS:

1-10 drops under the tongue, 2 times a day or as directed by a health professional. Consult a physician for use in children under 12 years of age.

INACTIVE INGREDIENTS:

Demineralized water, 25% ethanol

QUESTIONS:

Dist. By: Deseret Biologicals, Inc.

469 W. Parkland Drive

Sandy, UT 84070

www.desbio.com

800-827-8204

PACKAGE LABEL DISPLAY:

Des Bio

Bio Lymph

Phase

Homeopathic

NDC 43742-1667-1

1 FL OZ (30 ml)